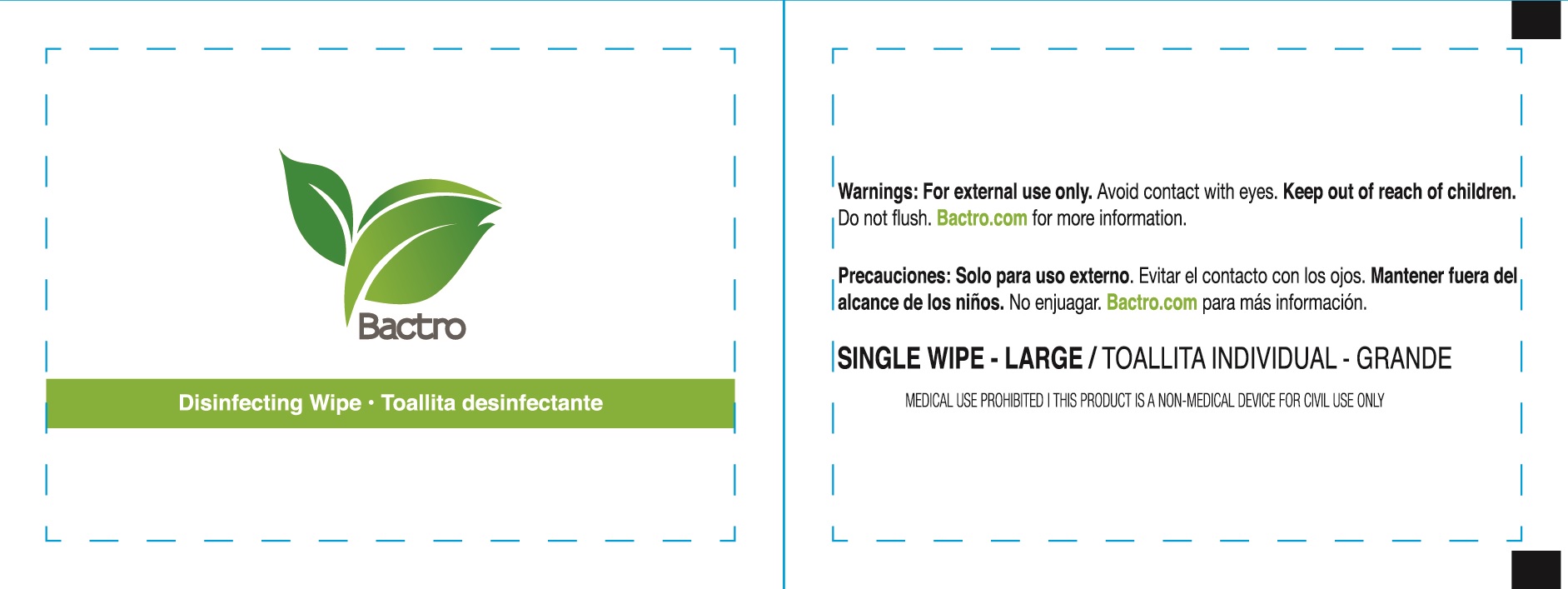 DRUG LABEL: Bactro Disinfecting  wipe
NDC: 71734-313 | Form: SWAB
Manufacturer: JIANGMEN SHUIZIRUN SANITARY ARTICLES CO., LTD.
Category: otc | Type: HUMAN OTC DRUG LABEL
Date: 20200710

ACTIVE INGREDIENTS: benzalkonium chloride 0.13 g/100 g
INACTIVE INGREDIENTS: water

DRUG FACTS

Active Ingredient

Benzalkonium Chloride .......... 0.13 %

Purpose

Antiseptic cleanser

Uses:

Apply topically as needed as cleanse

Warnings

DO NOT USE

For external use on hands only. Stop use and ask a doctor if irritation develops.

Store and handling

Store in a cool place.

Keep out of reach of children.

if swallowed get medical help or contact a Poison Control Center right away.

Directions

apply to skin as needed. Discard after single use.

Inactive Ingredients:

Glycerol,1,2-propanediol, 2-phenoxyetanol, Didecyl dimethyl ammonium chloride, 2-propandiol, Antibacterial synerists, Stabilizer, Water